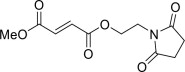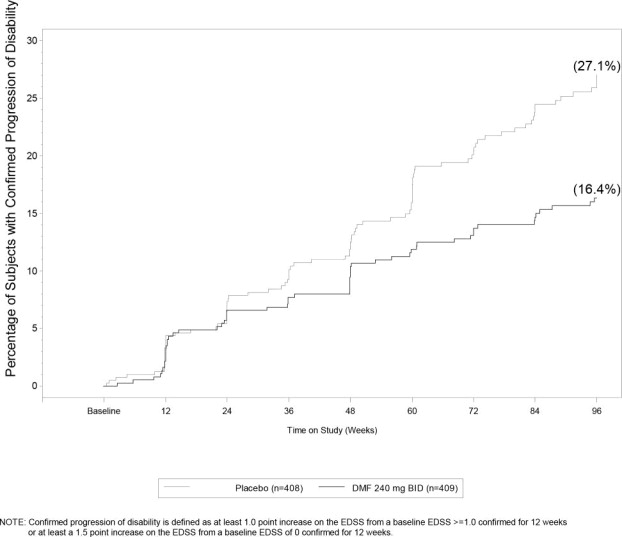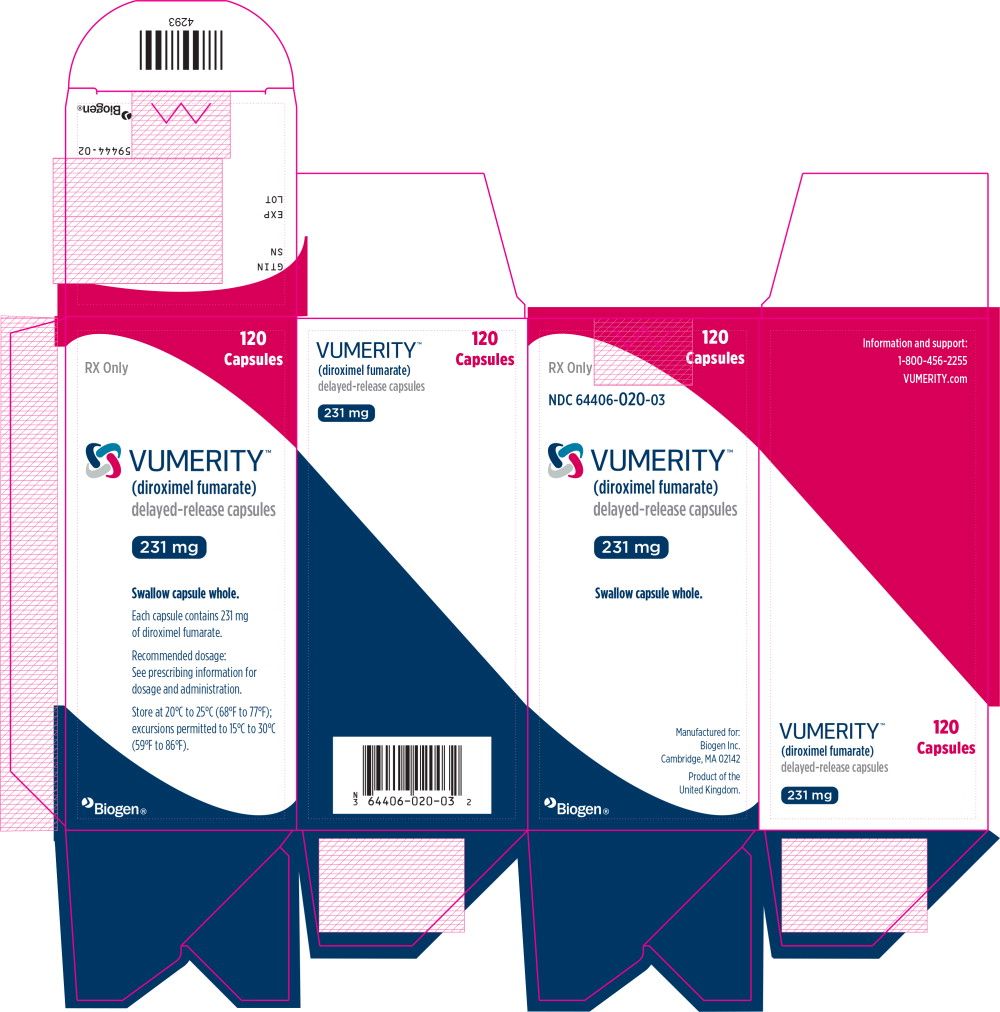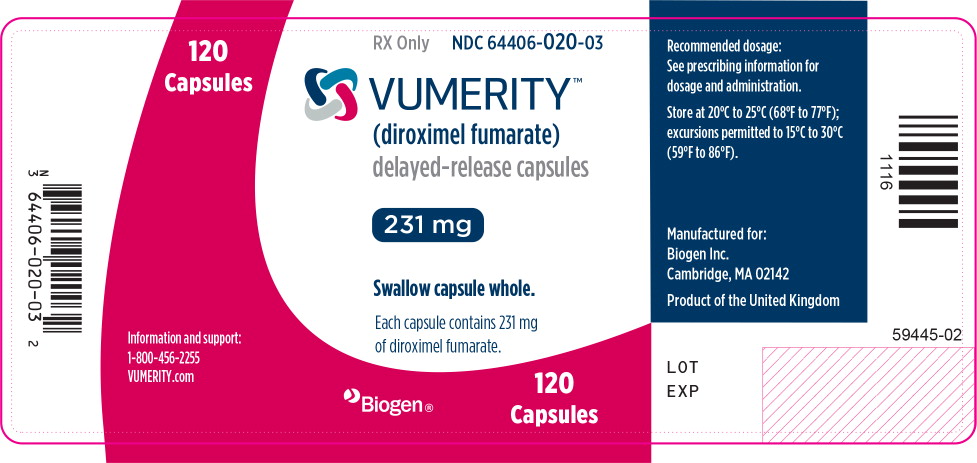 DRUG LABEL: Vumerity
NDC: 64406-020 | Form: CAPSULE
Manufacturer: Biogen Inc.
Category: prescription | Type: HUMAN PRESCRIPTION DRUG LABEL
Date: 20250529

ACTIVE INGREDIENTS: diroximel fumarate 231 mg/1 1
INACTIVE INGREDIENTS: methacrylic acid and ethyl acrylate copolymer; crospovidone; microcrystalline cellulose; silicon dioxide; triethyl citrate; talc; magnesium stearate; hypromellose, unspecified; titanium dioxide; potassium chloride; carrageenan

HIGHLIGHTS OF PRESCRIBING INFORMATION

These highlights do not include all the information needed to use VUMERITY® safely and effectively. See full prescribing information for VUMERITY.
VUMERITY® (diroximel fumarate) delayed-release capsules, for oral use
Initial U.S. Approval: 2013

RECENT MAJOR CHANGES

Warnings and Precautions, Serious Gastrointestinal Reactions (5.7) | 12/2023

1 INDICATIONS AND USAGE

VUMERITY is indicated for the treatment of relapsing forms of multiple sclerosis (MS), to include clinically isolated syndrome, relapsing-remitting disease, and active secondary progressive disease, in adults. (1)

2 DOSAGE AND ADMINISTRATION

- Blood tests are required prior to initiation of VUMERITY (2.1)
- Starting dose: 231 mg twice a day, orally, for 7 days (2.2)
- Maintenance dose after 7 days: 462 mg (administered as two 231 mg capsules) twice a day, orally (2.2)
- Swallow VUMERITY capsules whole and intact. Do not crush, chew, or sprinkle capsule contents on food (2.3)
- Avoid administration of VUMERITY with a high-fat, high-calorie meal/snack (2.3)
- Avoid co-administration of VUMERITY with alcohol (2.3)

3 DOSAGE FORMS AND STRENGTHS

Delayed-release capsules: 231 mg (3)

4 CONTRAINDICATIONS

- Known hypersensitivity to diroximel fumarate, dimethyl fumarate, or to any of the excipients of VUMERITY (4)
- Co-administration with dimethyl fumarate (4)

5 WARNINGS AND PRECAUTIONS

- Anaphylaxis and Angioedema: Discontinue and do not restart VUMERITY if these occur. (5.1)
- Progressive Multifocal Leukoencephalopathy (PML): Withhold VUMERITY at the first sign or symptom suggestive of PML. (5.2)
- Herpes Zoster and Other Serious Opportunistic Infections: Consider withholding VUMERITY in cases of serious infection until the infection has resolved. (5.3)
- Lymphopenia: Obtain a CBC including lymphocyte count before initiating VUMERITY, after 6 months, and every 6 to 12 months thereafter. Consider interruption of VUMERITY if lymphocyte counts <0.5 × 10^9/L persist for more than six months. (5.4)
- Liver Injury: Obtain serum aminotransferase, alkaline phosphatase, and total bilirubin levels before initiating VUMERITY and during treatment, as clinically indicated. Discontinue VUMERITY if clinically significant liver injury induced by VUMERITY is suspected. (5.6)

6 ADVERSE REACTIONS

Most common adverse reactions (incidence for dimethyl fumarate [which has the same active metabolite as VUMERITY] ≥10% and ≥2% more than placebo) were flushing, abdominal pain, diarrhea, and nausea. (6.1)

To report SUSPECTED ADVERSE REACTIONS, contact Biogen at 1-800-456-2255 or FDA at 1-800-FDA-1088 or www.fda.gov/medwatch.

8 USE IN SPECIFIC POPULATIONS

- Pregnancy: Based on animal data, may cause fetal harm. (8.1)
- VUMERITY is not recommended in patients with moderate or severe renal impairment. (8.6)

FULL PRESCRIBING INFORMATION

1 INDICATIONS AND USAGE

VUMERITY is indicated for the treatment of relapsing forms of multiple sclerosis (MS), to include clinically isolated syndrome, relapsing-remitting disease, and active secondary progressive disease, in adults.

2 DOSAGE AND ADMINISTRATION

2.1 Blood Tests Prior to Initiation of VUMERITY

Obtain the following prior to treatment with VUMERITY:

- A complete blood cell count (CBC), including lymphocyte count [see Warnings and Precautions (5.4)].
- Serum aminotransferase, alkaline phosphatase, and total bilirubin levels [see Warnings and Precautions (5.5)].

2.2 Dosing Information

The starting dosage for VUMERITY is 231 mg twice a day orally. After 7 days, the dosage should be increased to the maintenance dosage of 462 mg (administered as two 231 mg capsules) twice a day orally. Temporary dosage reductions to 231 mg twice a day may be considered for individuals who do not tolerate the maintenance dosage. Within 4 weeks, the recommended dosage of 462 mg twice a day should be resumed. Discontinuation of VUMERITY should be considered for patients unable to tolerate return to the maintenance dosage. Administration of non-enteric coated aspirin (up to a dose of 325 mg) 30 minutes prior to VUMERITY dosing may reduce the incidence or severity of flushing [see Clinical Pharmacology (12.3)].

2.3 Administration Instructions

Swallow VUMERITY capsules whole and intact. Do not crush or chew, or sprinkle the capsule contents on food.

If taken with food, avoid a high-fat, high-calorie meal/snack; the meal/snack should contain no more than 700 calories and no more than 30 g fat [see Warnings and Precautions (5.6) and Clinical Pharmacology (12.3)].

Avoid co-administration of VUMERITY with alcohol [see Clinical Pharmacology (12.3)].

2.4 Blood Tests to Assess Safety After Initiation of VUMERITY

Obtain a complete blood cell count (CBC), including lymphocyte count, 6 months after initiation of VUMERITY and then every 6 to 12 months thereafter, as clinically indicated [see Warnings and Precautions (5.4)].

Obtain serum aminotransferase, alkaline phosphatase, and total bilirubin levels during treatment with VUMERITY, as clinically indicated [see Warnings and Precautions (5.5)].

2.5 Patients With Renal Impairment

No dosing adjustment is recommended in patients with mild renal impairment.

VUMERITY is not recommended in patients with moderate or severe renal impairment [see Use in Specific Populations (8.6) and Clinical Pharmacology (12.3)].

3 DOSAGE FORMS AND STRENGTHS

VUMERITY is available as hard, delayed-release capsules containing 231 mg of diroximel fumarate. The capsules have a white cap and a white body, printed with “DRF 231 mg” in black ink on the body.

4 CONTRAINDICATIONS

VUMERITY is contraindicated in patients

- With known hypersensitivity to diroximel fumarate, dimethyl fumarate, or to any of the excipients of VUMERITY. Reactions may include anaphylaxis and angioedema [see Warnings and Precautions (5.1)].
- Taking dimethyl fumarate [see Drug Interactions (7.1)].

5 WARNINGS AND PRECAUTIONS

5.1 Anaphylaxis and Angioedema

VUMERITY can cause anaphylaxis and angioedema after the first dose or at any time during treatment. Signs and symptoms in patients taking dimethyl fumarate (which has the same active metabolite as VUMERITY) have included difficulty breathing, urticaria, and swelling of the throat and tongue. Patients should be instructed to discontinue VUMERITY and seek immediate medical care should they experience signs and symptoms of anaphylaxis or angioedema.

5.2 Progressive Multifocal Leukoencephalopathy

Progressive multifocal leukoencephalopathy (PML) has occurred in patients with MS treated with dimethyl fumarate (which has the same active metabolite as VUMERITY). PML is an opportunistic viral infection of the brain caused by the JC virus (JCV) that typically only occurs in patients who are immunocompromised, and that usually leads to death or severe disability. A fatal case of PML occurred in a patient who received dimethyl fumarate for 4 years while enrolled in a clinical trial. During the clinical trial, the patient experienced prolonged lymphopenia (lymphocyte counts predominantly <0.5 × 10^9/L for 3.5 years) while taking dimethyl fumarate [see Warnings and Precautions (5.4)]. The patient had no other identified systemic medical conditions resulting in compromised immune system function and had not previously been treated with natalizumab, which has a known association with PML. The patient was also not taking any immunosuppressive or immunomodulatory medications concomitantly.

PML has also occurred in patients taking dimethyl fumarate in the postmarketing setting in the presence of lymphopenia (<0.9 × 10^9/L). While the role of lymphopenia in these cases is uncertain, the PML cases have occurred predominantly in patients with lymphocyte counts <0.8×10^9/L persisting for more than 6 months.

At the first sign or symptom suggestive of PML, withhold VUMERITY and perform an appropriate diagnostic evaluation. Typical symptoms associated with PML are diverse, progress over days to weeks, and include progressive weakness on one side of the body or clumsiness of limbs, disturbance of vision, and changes in thinking, memory, and orientation leading to confusion and personality changes.

Magnetic resonance imaging (MRI) findings may be apparent before clinical signs or symptoms. Cases of PML diagnosed based on MRI findings and the detection of JCV DNA in the cerebrospinal fluid in the absence of clinical signs or symptoms specific to PML, have been reported in patients treated with other MS medications associated with PML. Many of these patients subsequently became symptomatic with PML. Therefore, monitoring with MRI for signs that may be consistent with PML may be useful, and any suspicious findings should lead to further investigation to allow for an early diagnosis of PML, if present. Lower PML-related mortality and morbidity have been reported following discontinuation of another MS medication associated with PML in patients with PML who were initially asymptomatic compared to patients with PML who had characteristic clinical signs and symptoms at diagnosis. It is not known whether these differences are due to early detection and discontinuation of MS treatment or due to differences in disease in these patients.

5.3 Herpes Zoster and Other Serious Opportunistic Infections

Serious cases of herpes zoster have occurred in patients treated with dimethyl fumarate (which has the same active metabolite as VUMERITY) including disseminated herpes zoster, herpes zoster ophthalmicus, herpes zoster meningoencephalitis, and herpes zoster meningomyelitis. These events may occur at any time during treatment. Monitor patients on VUMERITY for signs and symptoms of herpes zoster. If herpes zoster occurs, appropriate treatment for herpes zoster should be administered.

Other serious opportunistic infections have occurred with dimethyl fumarate, including cases of serious viral (herpes simplex virus, West Nile virus, cytomegalovirus), fungal (Candida and Aspergillus), and bacterial (Nocardia, Listeria monocytogenes, Mycobacterium tuberculosis) infections. These infections have been reported in patients with reduced absolute lymphocyte counts (ALC) as well as in patients with normal ALC. These infections have affected the brain, meninges, spinal cord, gastrointestinal tract, lungs, skin, eye, and ear. Patients with symptoms and signs consistent with any of these infections should undergo prompt diagnostic evaluation and receive appropriate treatment.

Consider withholding VUMERITY treatment in patients with herpes zoster or other serious infections until the infection has resolved [see Adverse Reactions (6.2)].

5.4 Lymphopenia

VUMERITY may decrease lymphocyte counts. In the MS placebo-controlled trials with dimethyl fumarate (which has the same active metabolite as VUMERITY), mean lymphocyte counts decreased by approximately 30% during the first year of treatment with dimethyl fumarate and then remained stable. Four weeks after stopping dimethyl fumarate, mean lymphocyte counts increased but did not return to baseline. Six percent (6%) of dimethyl fumarate patients and <1% of placebo patients experienced lymphocyte counts <0.5 × 10^9/L (lower limit of normal 0.91 × 10^9/L). The incidence of infections (60% vs 58%) and serious infections (2% vs 2%) was similar in patients treated with dimethyl fumarate or placebo, respectively. There was no increased incidence of serious infections observed in patients with lymphocyte counts <0.8 × 10^9/L or ≤0.5 × 10^9/L in controlled trials, although one patient in an extension study developed PML in the setting of prolonged lymphopenia (lymphocyte counts predominantly <0.5 × 10^9/L for 3.5 years) [see Warnings and Precautions (5.2)].

In controlled and uncontrolled clinical trials with dimethyl fumarate, 2% of patients experienced prolonged, severe lymphopenia, (defined as lymphocyte counts <0.5 x 10^9/L for at least six months); in this group of patients, the majority of lymphocyte counts remained <0.5 x 10^9/L with continued therapy. In these patients with prolonged, severe lymphopenia, the median time for lymphocyte counts to return to normal after discontinuing dimethyl fumarate was 96.0 weeks.

In these controlled and uncontrolled clinical studies, among patients who did not experience prolonged, severe lymphopenia during treatment, the median times for lymphocyte counts to return to normal after discontinuing dimethyl fumarate were as follows:

- 4.3 weeks in patients with mild lymphopenia (lymphocyte count ≥0.8 x 10^9/L) at discontinuation,
- 10.0 weeks in patients with moderate lymphopenia (lymphocyte count 0.5 to <0.8 x 10^9/L) at discontinuation, and
- 16.7 weeks in patients with severe lymphopenia (lymphocyte count <0.5 x 10^9/L) at discontinuation.

Neither VUMERITY nor dimethyl fumarate have been studied in patients with preexisting low lymphocyte counts.

Obtain a complete blood count (CBC), including lymphocyte count, before initiating treatment with VUMERITY, 6 months after starting treatment, and then every 6 to 12 months thereafter, and as clinically indicated. Consider interruption of VUMERITY in patients with lymphocyte counts less than 0.5 × 10^9/L persisting for more than six months. Given the potential for delayed recovery of lymphocyte counts, continue to obtain lymphocyte counts until their recovery if VUMERITY is discontinued or interrupted because of lymphopenia. Consider withholding treatment from patients with serious infections until resolution. Decisions about whether or not to restart VUMERITY should be individualized based on clinical circumstances.

5.5 Liver Injury

Clinically significant cases of liver injury have been reported in patients treated with dimethyl fumarate (which has the same active metabolite as VUMERITY) in the postmarketing setting. The onset has ranged from a few days to several months after initiation of treatment with dimethyl fumarate. Signs and symptoms of liver injury, including elevation of serum aminotransferases to greater than 5-fold the upper limit of normal and elevation of total bilirubin to greater than 2-fold the upper limit of normal have been observed. These abnormalities resolved upon treatment discontinuation. Some cases required hospitalization. None of the reported cases resulted in liver failure, liver transplant, or death. However, the combination of new serum aminotransferase elevations with increased levels of bilirubin caused by drug-induced hepatocellular injury is an important predictor of serious liver injury that may lead to acute liver failure, liver transplant, or death in some patients.

Elevations of hepatic transaminases (most no greater than 3 times the upper limit of normal) were observed during controlled trials with dimethyl fumarate [see Adverse Reactions (6.1)].

Obtain serum aminotransferase, alkaline phosphatase (ALP), and total bilirubin levels prior to treatment with VUMERITY and during treatment, as clinically indicated. Discontinue VUMERITY if clinically significant liver injury induced by VUMERITY is suspected.

5.6 Flushing

VUMERITY may cause flushing (e.g., warmth, redness, itching, and/or burning sensation). In clinical trials of dimethyl fumarate (which has the same active metabolite as VUMERITY), 40% of dimethyl fumarate-treated patients experienced flushing. Flushing symptoms generally began soon after initiating dimethyl fumarate and usually improved or resolved over time. In the majority of patients who experienced flushing, it was mild or moderate in severity. Three percent (3%) of patients discontinued dimethyl fumarate for flushing and <1% had serious flushing symptoms that were not life-threatening but led to hospitalization.

Administration of VUMERITY with food may reduce the incidence of flushing [see Dosage and Administration (2.3)]. Studies with dimethyl fumarate show that administration of non-enteric coated aspirin (up to a dose of 325 mg) 30 minutes prior to dosing may reduce the incidence or severity of flushing [see Clinical Pharmacology (12.3)].

5.7 Serious Gastrointestinal Reactions

Serious gastrointestinal reactions, including perforation, ulceration, hemorrhage, and obstruction, some with fatal outcomes, have been reported in the postmarketing setting with the use of fumaric acid esters, including VUMERITY, with or without concomitant aspirin use. The majority of these events have occurred within 6 months of fumaric acid ester treatment initiation. In controlled clinical trials, the incidence of serious gastrointestinal adverse reactions was 1% in patients treated with dimethyl fumarate; these events, none of which were fatal, included vomiting (0.3%) and abdominal pain (0.3%) [see Adverse Reactions (6.1)].

Monitor patients, promptly evaluate, and discontinue VUMERITY for new or worsening severe gastrointestinal signs and symptoms.

6 ADVERSE REACTIONS

The following important adverse reactions are described elsewhere in labeling:

- Anaphylaxis and Angioedema [see Warnings and Precautions (5.1)]
- Progressive Multifocal Leukoencephalopathy [see Warnings and Precautions Section (5.2)]
- Herpes Zoster and Other Serious Opportunistic Infections [see Warnings and Precautions (5.3)]
- Lymphopenia [see Warnings and Precautions (5.4)]
- Liver Injury [see Warnings and Precautions (5.6)]
- Flushing [see Warnings and Precautions (5.6)]
- Serious Gastrointestinal Reactions [see Warnings and Precautions (5.7)]

6.1 Clinical Trials Experience

Because clinical trials are conducted under widely varying conditions, adverse reaction rates observed in clinical trials of a drug cannot be directly compared to rates in the clinical trials of another drug and may not reflect the rates observed in clinical practice.

The data described in the following sections were obtained using dimethyl fumarate delayed-release capsules, which has the same active metabolite as VUMERITY.

In placebo controlled and uncontrolled clinical studies of dimethyl fumarate (which has the same active metabolite as VUMERITY), a total of 2513 patients have been followed for periods up to 13 years with an overall exposure equivalent to 11,318 person-years. A total of 1169 patients have received at least 5 years of treatment with dimethyl fumarate, and 426 patients have received at least 10 years of treatment with dimethyl fumarate.

Adverse Reactions in Placebo-Controlled Trials with Dimethyl Fumarate

In the two well-controlled studies demonstrating effectiveness, 1529 patients received dimethyl fumarate with an overall exposure of 2244 person-years [see Clinical Studies (14)].

The adverse reactions presented in Table 1 below are based on safety information from 769 patients treated with dimethyl fumarate 240 mg twice a day and 771 placebo-treated patients. The most common adverse reactions (incidence ≥10% and ≥2% more than placebo) for dimethyl fumarate were flushing, abdominal pain, diarrhea, and nausea.

Table 1: Adverse Reactions in Study 1 and 2 Reported for Dimethyl Fumarate at ≥2% Higher Incidence than Placebo
Adverse Reactions | Dimethyl Fumarate 240 mg Twice Daily (N=769) % | Placebo (N=771) %
Flushing | 40 | 6
Abdominal pain | 18 | 10
Diarrhea | 14 | 11
Nausea | 12 | 9
Vomiting | 9 | 5
Pruritus | 8 | 4
Rash | 8 | 3
Albumin urine present | 6 | 4
Erythema | 5 | 1
Dyspepsia | 5 | 3
Aspartate aminotransferase increased | 4 | 2
Lymphopenia | 2 | <1

Gastrointestinal

Dimethyl fumarate caused GI events (e.g., nausea, vomiting, diarrhea, abdominal pain, and dyspepsia). The incidence of GI events was higher early in the course of treatment (primarily in month 1) and usually decreased over time in patients treated with dimethyl fumarate compared with placebo. Four percent (4%) of patients treated with dimethyl fumarate and less than 1% of placebo patients discontinued due to gastrointestinal events. The incidence of serious GI events was 1% in clinical trial patients treated with dimethyl fumarate; these events, none of which were fatal, included vomiting (0.3%) and abdominal pain (0.3%).

Hepatic Transaminases

An increased incidence of elevations of hepatic transaminases in patients treated with dimethyl fumarate was seen primarily during the first six months of treatment, and most patients with elevations had levels <3 times the upper limit of normal (ULN) during controlled trials. Elevations of alanine aminotransferase and aspartate aminotransferase to ≥3 times the ULN occurred in a small number of patients treated with both dimethyl fumarate and placebo and were balanced between groups. There were no elevations in transaminases ≥3 times the ULN with concomitant elevations in total bilirubin >2 times the ULN. Discontinuations due to elevated hepatic transaminases were <1% and were similar in patients treated with dimethyl fumarate or placebo.

Eosinophilia

A transient increase in mean eosinophil counts was seen during the first 2 months of therapy.

Adverse Reactions in Clinical Studies with VUMERITY

In clinical studies assessing safety in patients with RRMS, approximately 700 patients were treated with VUMERITY and approximately 490 patients received more than 1 year of treatment with VUMERITY. The adverse reaction profile of VUMERITY was consistent with the experience in the placebo-controlled clinical trials with dimethyl fumarate.

6.2 Postmarketing Experience

The following adverse reaction has been identified during post approval use of dimethyl fumarate. Because these reactions are reported voluntarily from a population of uncertain size, it is not always possible to reliably estimate their frequency or establish a causal relationship to drug exposure.

Gastrointestinal Disorders: Acute pancreatitis; Gastrointestinal perforation, ulceration, obstruction, and hemorrhage [see Warnings and Precautions (5.7)]

Hepatobiliary Disorders: Liver function abnormalities (elevations in transaminases ≥3 times ULN with concomitant elevations in total bilirubin >2 times ULN) [see Warnings and Precautions (5.5)].

Infections and Infestations: Herpes zoster infection and other serious opportunistic infections [See Warnings and Precautions (5.3)].

Respiratory, Thoracic, and Mediastinal Disorders: Rhinorrhea

Skin and Subcutaneous: Alopecia

7 DRUG INTERACTIONS

7.1 Concomitant Dimethyl Fumarate

VUMERITY is contraindicated in patients currently taking dimethyl fumarate, which is also metabolized to monomethyl fumarate. VUMERITY may be initiated the day following discontinuation of dimethyl fumarate [see Contraindications (4)].

8 USE IN SPECIFIC POPULATIONS

8.1 Pregnancy

Pregnancy Exposure Registry

There is a pregnancy exposure registry that monitors pregnancy outcomes in women exposed to VUMERITY during pregnancy. Encourage patients to enroll by calling 1-833-569-2635 or visiting www.vumeritypregnancyregistry.com.

Risk Summary

There are no adequate data on the developmental risk associated with the use of VUMERITY in pregnant women. Available data from a pregnancy registry for dimethyl fumarate (which has the same active metabolite as VUMERITY), observational studies, and pharmacovigilance pertaining to dimethyl fumarate use in pregnant women have not indicated an increased risk of major birth defects, miscarriage, or other adverse maternal or fetal outcomes. Most of the reported exposures to dimethyl fumarate occurred during the first trimester of pregnancy (see Data). In animal studies, administration of diroximel fumarate during pregnancy or throughout pregnancy and lactation resulted in adverse effects on embryofetal and offspring development (increased incidences of skeletal abnormalities, increased mortality, decreased body weights, neurobehavioral impairment) at clinically relevant drug exposures [see Data].

The background risk of major birth defects and miscarriage for the indicated population is unknown. All pregnancies have a background risk of birth defect, loss, or other adverse outcomes. In the U.S. general population, the estimated background risk of major birth defects and miscarriage in clinically recognized pregnancies is 2-4% and 15-20%, respectively.

Data

Human Data

In a prospective observational pregnancy registry for dimethyl fumarate (2013-2022), the rate of major birth defects among 362 live births and stillbirths from women who were exposed to dimethyl fumarate during pregnancy was 3.6% (95% CI: 1.9-6.1). No specific pattern of major birth defects was identified. Important potential study limitations include exposure misclassification, no adjustment for confounders, and lack of an internal comparator cohort.

Animal Data

Oral administration of diroximel fumarate (0, 40, 100, or 400 mg/kg/day) to pregnant rats throughout organogenesis resulted in a decrease in fetal body weight and an increase in fetal skeletal variations at the highest dose tested, which was associated with maternal toxicity. Plasma exposures (AUC) for MMF and HES (the major circulating drug-related compound in humans) at the no-effect dose (100 mg/kg/day) for adverse effects on embryofetal development were approximately 2 times those in humans at the recommended human dose (RHD) of 924 mg/day.

Oral administration of diroximel fumarate (0, 50, 150, or 350 mg/kg/day) to pregnant rabbits throughout organogenesis resulted in an increase in fetal skeletal malformations at the mid and high doses and reduced fetal body weight and increases in embryofetal death and fetal skeletal variations at the highest dose tested. The high dose was associated with maternal toxicity. Plasma exposures (AUC) for MMF and HES at the no-effect dose (50 mg/kg/day) for adverse effects on embryofetal development were similar to (MMF) or less than (HES) those in humans at the RHD.

Oral administration of diroximel fumarate (0, 40, 100, or 400 mg/kg/day) to rats throughout gestation and lactation resulted in reduced weight, which persisted into adulthood, and adverse effects on neurobehavioral function in offspring at the highest dose tested. Plasma exposures (AUC) for MMF and HES at the no-effect dose for adverse effects on postnatal development (100 mg/kg/day) were approximately 3 times (MMF) or similar to (HES) those in humans at the RHD.

8.2 Lactation

Risk Summary

There are no data on the presence of diroximel fumarate or metabolites (MMF, HES) in human milk. The effects on the breastfed infant and on milk production are unknown.

The developmental and health benefits of breastfeeding should be considered along with the mother's clinical need for VUMERITY and any potential adverse effects on the breastfed infant from the drug or from the underlying maternal condition.

8.4 Pediatric Use

Safety and effectiveness in pediatric patients have not been established.

8.5 Geriatric Use

Clinical studies of dimethyl fumarate and VUMERITY did not include sufficient numbers of patients aged 65 years and over to determine whether they respond differently from younger patients.

8.6 Renal Impairment

No dosage adjustment is necessary in patients with mild renal impairment. Because of an increase in the exposure of a major metabolite [2-hydroxyethyl succinimide (HES)], use of VUMERITY is not recommended in patients with moderate or severe renal impairment [see Clinical Pharmacology (12.3)].

11 DESCRIPTION

VUMERITY contains diroximel fumarate. The chemical name of diroximel fumarate is 2-Butenedioic acid (2E)-, 1-[2-(2,5-dioxo-1-pyrrolidinyl)ethyl] 4-methyl ester, which has a molecular formula of C11H13NO6 and molecular weight of 255.22. Diroximel fumarate has the following structure:

Diroximel fumarate is a white to off-white powder that is slightly soluble in water.

VUMERITY is provided as delayed-release capsules for oral administration. Each capsule contains 231 mg of diroximel fumarate and the following inactive ingredients: crospovidone, colloidal silicon dioxide, magnesium stearate (non-bovine), methacrylic acid and ethyl acrylate copolymer, microcrystalline cellulose, talc, and triethyl citrate.

The capsule shell contains carrageenan, hypromellose, potassium chloride, and titanium dioxide. It is printed with black ink that contains iron oxide, potassium hydroxide, propylene glycol, and shellac.

12 CLINICAL PHARMACOLOGY

12.1 Mechanism of Action

The mechanism by which diroximel fumarate exerts its therapeutic effect in multiple sclerosis is unknown. MMF, the active metabolite of diroximel fumarate, has been shown to activate the nuclear factor (erythroid-derived 2)-like 2 (Nrf2) pathway in vitro and in vivo in animals and humans. The Nrf2 pathway is involved in the cellular response to oxidative stress. MMF has been identified as a nicotinic acid receptor agonist in vitro.

12.2 Pharmacodynamics

Cardiac Electrophysiology

At a dose 2 times the maximum recommended dose, VUMERITY does not prolong the QTc interval to any clinically relevant extent.

12.3 Pharmacokinetics

After oral administration of VUMERITY, diroximel fumarate undergoes rapid presystemic hydrolysis by esterases and is converted to its active metabolite, monomethyl fumarate (MMF). Diroximel fumarate is not quantifiable in plasma following oral administration of VUMERITY. Therefore, all pharmacokinetic analyses related to VUMERITY were performed with plasma MMF concentrations. Pharmacokinetic data were obtained in subjects with relapsing forms of multiple sclerosis (MS) and healthy volunteers.

Absorption

Following oral administration of VUMERITY, the median tmax of MMF is 2.5 to 3 hours. The peak plasma concentration (Cmax) and overall exposure (AUC) increased dose proportionally in the recommended daily dose range (462 mg to 924 mg). Following administration of VUMERITY 462 mg in patients with MS, the mean Cmax of MMF was 2.11 mg/L. The mean steady state AUC of MMF was estimated to be 8.32 mg.hr/L following twice daily dosing in patients with MS.

Effect of Food

In an open-label, randomized, balanced, crossover study, co-administration of VUMERITY with a high-fat, high-calorie meal (900-1000 calories, 50% of calories from fat) did not affect the AUC of MMF, but resulted in an approximately 44% reduction in Cmax compared to fasted state [see Dosage and Administration (2.3)]. The MMF Cmax with low-fat, low-calorie (350 to 400 calories, 10 to 15 g fat) and medium-fat, medium-calorie (650 to 700 calories, 25 to 30 g fat) meals was reduced by approximately 12% and 25%, respectively.

Relative to fasted state, the tmax of MMF was delayed from 2.5 hours (fasted state) to 4.5 hours (low-fat, low-calorie meal or a medium-fat, medium-calorie meal) and 7.0 hours (high-fat, high-calorie meal) in the fed state. There was no impact of low, medium, or high-fat meals on the AUC of MMF after administration of VUMERITY.

Distribution

The apparent volume of distribution for MMF is between 72 L and 83 L in healthy subjects after administration of VUMERITY. Human plasma protein binding of MMF is 27-45% and independent of concentration.

Elimination

Metabolism

In humans, diroximel fumarate is extensively metabolized by esterases, which are ubiquitous in the gastrointestinal tract, blood, and tissues, to the major active metabolite, MMF, before it reaches the systemic circulation. Further metabolism of MMF occurs through the tricarboxylic acid (TCA) cycle, with no involvement of the cytochrome P450 (CYP) system. Fumaric and citric acid, and glucose are the major metabolites of MMF in plasma.

Esterase metabolism of diroximel fumarate also produces 2-hydroxyethyl succinimide (HES), an inactive major metabolite.

Excretion

MMF is mainly eliminated as carbon dioxide in the expired air with only trace amounts (less than 0.3% of the total dose) recovered in urine.

The terminal half-life of MMF is approximately 1 hour, and accumulation of MMF does not occur with multiple doses of VUMERITY.

HES is mainly eliminated in urine (58-63% of the dose was excreted as HES in urine).

Specific Populations

Age (18-79 years), sex, and race (White, African American, and Asian) did not have clinically meaningful effects on the pharmacokinetics of MMF after administration of VUMERITY. The effect of hepatic impairment or severe renal impairment (CrCl <30 mL/min, Cockcroft-Gault) requiring hemodialysis on MMF pharmacokinetics is unknown.

Patients with Renal Impairment

A single-dose clinical study investigating the effect of renal impairment on the pharmacokinetics of diroximel fumarate and its metabolites MMF and HES was conducted. The study included cohorts with mild, moderate, and severe renal impairment and a healthy cohort (8 subjects per cohort) and found no clinically relevant changes in MMF exposure. However, HES exposure increased by 1.3, 1.8, and 2.7-fold with mild, moderate, and severe renal impairment, respectively, compared to the healthy cohort [see Use in Specific Populations (8.6)]. There are no data available on long-term use of VUMERITY in patients with moderate or severe renal impairment.

Patients with Hepatic Impairment

No studies have been conducted in subjects with hepatic impairment. However, hepatic impairment would not be expected to affect exposure to MMF and therefore no dosage adjustment is necessary.

Drug Interaction Studies

Diroximel fumarate metabolism does not involve CYP enzymes, therefore, no clinically meaningful interactions are expected when administered with CYP inhibitors or inducers.

In vitro studies found diroximel fumarate and its metabolites did not inhibit CYP1A2, CYP2B6, CYP2C8, CYP2C9, CYP2C19, CYP2D6, and CYP3A4/5 enzymes in human liver microsomes or induce CYP1A2, 2B6, or 3A4/5 in cultured human hepatocytes.

Diroximel fumarate did not inhibit P-gp in vivo. The major circulating inactive metabolite of diroximel fumarate, HES, did not inhibit P-gp and was neither a substrate nor an inhibitor of BCRP, MATE1, MATE2-K, OAT1, OAT3, or OCT2.

Aspirin, when administered approximately 30 minutes before dimethyl fumarate, did not alter the pharmacokinetics of MMF.

Oral Contraceptives

In a study conducted with dimethyl fumarate, no relevant effects of MMF on oral contraceptive exposure were observed when administered with a combined oral contraceptive (norelgestromin and ethinyl estradiol). No interaction studies have been performed with oral contraceptives containing other progestogens.

Alcohol

Administration of VUMERITY at the same time with 5% v/v and 40% v/v ethanol did not alter total MMF exposure relative to administration with water, demonstrating that the coingestion of ethanol does not induce dose dumping. The mean peak plasma MMF concentration for diroximel fumarate was decreased by 9% and 21%, when co-administered with 240 mL of 5% v/v and 40% v/v of ethanol, respectively [see Dosage and Administration (2.3)].

Vaccines

A randomized, open-label study examined the concomitant use of dimethyl fumarate (which has the same active metabolite as VUMERITY) and several non-live vaccines in adults 27-55 years of age with relapsing forms of MS (38 subjects undergoing treatment with dimethyl fumarate at the time of vaccination and 33 subjects undergoing treatment with non-pegylated interferon at the time of vaccination). Concomitant exposure to dimethyl fumarate did not attenuate antibody responses to tetanus toxoid-containing vaccine, pneumococcal polysaccharide, and meningococcal vaccines relative to antibody responses in interferon-treated patients. The impact of these findings on vaccine effectiveness in this patient population is unknown. The safety and effectiveness of live or live-attenuated vaccines administered concomitantly with VUMERITY or dimethyl fumarate have not been assessed.

13 NONCLINICAL TOXICOLOGY

13.1 Carcinogenesis, Mutagenesis, Impairment of Fertility

Carcinogenesis

Oral administration of diroximel fumarate (0, 0, 30, 100, 300 or 1000 [females only] mg/kg/day) for 26 weeks to Tg.rasH2 mice resulted in no drug-related tumors.

Oral administration of diroximel fumarate (0, 0, 15, 50, or 150 mg/kg/day) to male and female rats resulted in an increase in tumors (Leydig cell adenomas of the testes) in males at the highest dose tested. At the higher dose (50 mg/kg/day) not associated with drug-related tumors, plasma exposures for MMF and HES (the major circulating drug-related compound in humans) were similar to (MMF) and less than (HES) those in humans at the recommended human dose (RHD) of 924 mg/day.

Mutagenesis

Diroximel fumarate was negative in the in vitro bacterial reverse mutation and in vivo rat micronucleus and comet assays. Diroximel fumarate was clastogenic (in the absence and presence of metabolic activation) in the in vitro chromosomal aberration assay in human peripheral blood lymphocytes.

Impairment of Fertility

No adverse effects on fertility were observed following oral administration of diroximel fumarate to male rats (0, 40, 120, or 400 mg/kg/day) prior to and during mating with untreated females and, in a separate study, to female rats (0, 40, 120, or 450 mg/kg/day) prior to and during mating with untreated males and continuing to Gestation Day (GD) 7. At the highest doses tested, plasma exposures (AUC) for MMF were approximately 7-9 times that in humans at the RHD. Plasma levels of HES were not quantitated.

13.2 Animal Toxicology and/or Pharmacology

Kidney toxicity, including tubular changes (degeneration, necrosis, regeneration, hypertrophy) and/or interstitial fibrosis, were observed following oral administration of diroximel fumarate in rats and monkeys. In the chronic toxicology study in rats (0, 50, 100, or 300 mg/kg/day), adverse renal findings occurred at all doses tested. Plasma exposures (AUC) at the low dose (50 mg/kg/day) were similar to (MMF) or less than (HES) those in humans at the RHD. In the chronic toxicology study in monkeys (0, 15, 50, or 150 mg/kg/day), adverse renal findings occurred at all but the lowest dose tested (15 mg/kg/day), which was associated with plasma MMF and HES exposures (AUC) less than those in humans at the RHD.

14 CLINICAL STUDIES

The efficacy of VUMERITY is based upon bioavailability studies in patients with relapsing forms of multiple sclerosis and healthy subjects comparing oral dimethyl fumarate delayed-release capsules to VUMERITY delayed-release capsules [see Clinical Pharmacology (12.3)].

The clinical studies described below were conducted using dimethyl fumarate.

The efficacy and safety of dimethyl fumarate were demonstrated in two studies (Studies 1 and 2) that evaluated dimethyl fumarate taken either twice or three times a day in patients with relapsing-remitting multiple sclerosis (RRMS). The starting dose for dimethyl fumarate was 120 mg twice or three times a day for the first 7 days, followed by an increase to 240 mg twice or three times a day. Both studies included patients who had experienced at least 1 relapse over the year preceding the trial or had a brain Magnetic Resonance Imaging (MRI) scan demonstrating at least one gadolinium-enhancing (Gd+) lesion within 6 weeks of randomization. The Expanded Disability Status Scale (EDSS) was also assessed and patients could have scores ranging from 0 to 5. Neurological evaluations were performed at baseline, every 3 months, and at the time of suspected relapse. MRI evaluations were performed at baseline, month 6, and year 1 and 2 in a subset of patients (44% in Study 1 and 48% in Study 2).

Study 1: Placebo-Controlled Trial in RRMS

Study 1 was a 2-year randomized, double-blind, placebo-controlled study in 1234 patients with RRMS. The primary endpoint was the proportion of patients relapsed at 2 years. Additional endpoints at 2 years included the number of new or newly enlarging T2 hyperintense lesions, number of new T1 hypointense lesions, number of Gd+ lesions, annualized relapse rate (ARR), and time to confirmed disability progression. Confirmed disability progression was defined as at least a 1 point increase from baseline EDSS (1.5 point increase for patients with baseline EDSS of 0) sustained for 12 weeks.

Patients were randomized to receive dimethyl fumarate 240 mg twice a day (n=410), dimethyl fumarate 240 mg three times a day (n=416), or placebo (n=408) for up to 2 years. The median age was 39 years, median time since diagnosis was 4 years, and median EDSS score at baseline was 2. The median time on study drug for all treatment arms was 96 weeks. The percentages of patients who completed 96 weeks on study drug per treatment group were 69% for patients assigned to dimethyl fumarate 240 mg twice a day, 69% for patients assigned to dimethyl fumarate 240 mg three times a day, and 65% for patients assigned to placebo groups.

Dimethyl fumarate had a statistically significant effect on all of the endpoints described above and the 240 mg three times daily dose showed no additional benefit over the dimethyl fumarate 240 mg twice daily dose. The results for this study (240 mg twice a day vs. placebo) are shown in Table 2 and Figure 1.

Table 2: Clinical and MRI Results of Study 1
 | Dimethyl Fumarate 240 mg BID | Placebo | P-value
Clinical Endpoints | N=410 | N=408
Proportion relapsing (primary endpoint) | 27% | 46% | <0.0001
Relative risk reduction | 49%
Annualized relapse rate | 0.172 | 0.364 | <0.0001
Relative reduction | 53%
Proportion with disability progression | 16% | 27% | 0.0050
Relative risk reduction | 38%
MRI Endpoints | N=152 | N=165
Mean number of new or newly enlarging T2 lesions over 2 years | 2.6 | 17 | <0.0001
Percentage of subjects with no new or newly enlarging lesions | 45% | 27%
Number of Gd+ lesions at 2 years Mean (median) | 0.1 (0) | 1.8 (0)
Percentage of subjects with
0 lesions | 93% | 62%
1 lesion | 5% | 10%
2 lesions | <1% | 8%
3 to 4 lesions | 0 | 9%
5 or more lesions | <1% | 11%
Relative odds reduction (percentage) | 90% |  | <0.0001
Mean number of new T1 hypointense lesions over 2 years | 1.5 | 5.6 | <0.0001

Figure 1: Time to 12-Week Confirmed Progression of Disability (Study 1)

Study 2: Placebo-Controlled Trial in RRMS

Study 2 was a 2-year multicenter, randomized, double-blind, placebo-controlled study that also included an open-label comparator arm in patients with RRMS. The primary endpoint was the annualized relapse rate at 2 years. Additional endpoints at 2 years included the number of new or newly enlarging T2 hyperintense lesions, number of T1 hypointense lesions, number of Gd+ lesions, proportion of patients relapsed, and time to confirmed disability progression as defined in Study 1.

Patients were randomized to receive dimethyl fumarate 240 mg twice a day (n=359), dimethyl fumarate 240 mg three times a day (n=345), an open-label comparator (n=350), or placebo (n=363) for up to 2 years. The median age was 37 years, median time since diagnosis was 3 years, and median EDSS score at baseline was 2.5. The median time on study drug for all treatment arms was 96 weeks. The percentages of patients who completed 96 weeks on study drug per treatment group were 70% for patients assigned to dimethyl fumarate 240 mg twice a day, 72% for patients assigned to dimethyl fumarate 240 mg three times a day, and 64% for patients assigned to placebo groups.

Dimethyl fumarate had a statistically significant effect on the relapse and MRI endpoints described above. There was no statistically significant effect on disability progression. The dimethyl fumarate 240 mg three times daily dose resulted in no additional benefit over the dimethyl fumarate 240 mg twice daily dose. The results for this study (240 mg twice a day vs. placebo) are shown in Table 3.

Table 3: Clinical and MRI Results of Study 2
 | Dimethyl Fumarate 240 mg BID | Placebo | P-value
Clinical Endpoints | N=359 | N=363
Annualized relapse rate | 0.224 | 0.401 | <0.0001
Relative reduction | 44%
Proportion relapsing | 29% | 41% | 0.0020
Relative risk reduction | 34%
Proportion with disability progression | 13% | 17% | 0.25
Relative risk reduction | 21%
MRI Endpoints | N=147 | N=144
Mean number of new or newly enlarging T2 lesions over 2 years | 5.1 | 17.4 | <0.0001
Percentage of subjects with no new or newly enlarging lesions | 27% | 12%
Number of Gd+ lesions at 2 years Mean (median) | 0.5 (0.0) | 2.0 (0.0)
Percentage of subjects with
0 lesions | 80% | 61%
1 lesion | 11% | 17%
2 lesions | 3% | 6%
3 to 4 lesions | 3% | 2%
5 or more lesions | 3% | 14%
Relative odds reduction (percentage) | 74% |  | <0.0001
Mean number of new T1 hypointense lesions over 2 years | 3.0 | 7.0 | <0.0001

16 HOW SUPPLIED/ STORAGE AND HANDLING

16.1 How Supplied

VUMERITY is available as delayed-release capsules for oral administration, containing 231 mg of diroximel fumarate. The 231 mg capsules have a white cap and a white body, printed with “DRF 231 mg” in black ink on the body. VUMERITY is available as follows:

Bottle of 120 capsules, NDC 64406-020-03.

16.2 Storage and Handling

Store at 20°C to 25°C (68°F to 77°F); excursions permitted to 15°C to 30°C (59°F to 86°F).

17 PATIENT COUNSELING INFORMATION

Advise the patient to read the FDA-approved patient labeling (Patient Information).

Dosage and Administration

Inform patients that they will take one capsule twice a day for the first 7 days and then two capsules twice a day thereafter. Advise patients to take VUMERITY as instructed. Inform patients to swallow VUMERITY capsules whole and intact. Inform patients to not crush, chew, or sprinkle capsule contents on food. Inform patients that they should avoid a high-fat, high-calorie meal/snack at the time they take VUMERITY. If taken with food, the meal/snack should contain no more than 700 calories and no more than 30 g fat. Advise patients to avoid co-administration of VUMERITY with alcohol [see Dosage and Administration (2.2)].

Anaphylaxis and Angioedema

Advise patients to discontinue VUMERITY and seek medical care if they develop signs and symptoms of anaphylaxis or angioedema [see Warnings and Precautions (5.1)].

Progressive Multifocal Leukoencephalopathy

Inform patients that progressive multifocal leukoencephalopathy (PML) has occured in patients who received dimethyl fumarate, and therefore may occur with VUMERITY. Inform the patient that PML is characterized by a progression of deficits and usually leads to death or severe disability over weeks or months. Inform the patient of the importance of contacting their healthcare provider if they develop any symptoms suggestive of PML. Inform the patient that typical symptoms associated with PML are diverse, progress over days to weeks, and include progressive weakness on one side of the body or clumsiness of limbs, disturbance of vision, and changes in thinking, memory, and orientation leading to confusion and personality changes [see Warnings and Precautions (5.2)].

Herpes Zoster and Other Serious Opportunistic Infections

Inform patients that herpes zoster and other serious opportunistic infections have occurred in patients who received dimethyl fumarate and therefore may occur with VUMERITY. Instruct the patient of the importance of contacting their doctor if they develop any signs or symptoms associated with herpes zoster or other serious opportunistic infections [see Warnings and Precautions (5.3)].

Lymphocyte Counts

Inform patients that VUMERITY may decrease lymphocyte counts. A blood test should be obtained before they start therapy. Blood tests are also recommended after 6 months of treatment, every 6 to 12 months thereafter, and as clinically indicated [see Warnings and Precautions (5.4) and Adverse Reactions (6.1)].

Liver Injury

Inform patients that VUMERITY may cause liver injury. Instruct patients treated with VUMERITY to report promptly to their healthcare provider any symptoms that may indicate liver injury, including fatigue, anorexia, right upper abdominal discomfort, dark urine, or jaundice. A blood test should be obtained before patients start therapy and during treatment, as clinically indicated [see Warnings and Precautions (5.5)].

Flushing

Inform patients that flushing is one of the most common reactions, especially at the initiation of therapy, and may decrease over time. Advise patients to contact their healthcare provider if they experience persistent and/or severe flushing. Advise patients experiencing flushing that taking VUMERITY with food (avoid high-fat, high-calorie meal or snack) or taking a non-enteric coated aspirin prior to taking VUMERITY may help [see Dosage and Administration (2.2) and Adverse Reactions (6.1)].

Gastrointestinal (GI) Reactions

Inform patients that GI events (abdominal pain, diarrhea, and nausea) are some of the most common adverse reactions, especially at the initiation of therapy, and may decrease over time. Some patients may experience more severe GI events, Advise patients to immediately contact their healthcare provider and discontinue VUMERITY if they experience gastrointestinal bleeding (e.g., rectal bleeding, bloody diarrhea, hematemesis) or other serious gastrointestinal adverse events (e.g., severe abdominal pain, severe vomiting and/or diarrhea) [see Warnings and Precautions (5.7)].

Pregnancy and Pregnancy Registry

Instruct patients that if they are pregnant or plan to become pregnant while taking VUMERITY they should inform their healthcare provider.

Encourage patients to enroll in the VUMERITY Pregnancy Registry if they become pregnant while taking VUMERITY [see Use in Specific Populations (8.1)].

PPI-54499-09

Manufactured for:
Biogen Inc.
Cambridge, MA 02142

VUMERITY is a registered trademark of Biogen.
© Biogen 2019 - 2024

Patient Information
VUMERITY (vue mer' i tee)
(diroximel fumarate) delayed-release capsules

What is VUMERITY?

- VUMERITY is a prescription medicine used to treat people with relapsing forms of multiple sclerosis (MS), to include clinically isolated syndrome, relapsing-remitting disease, and active secondary progressive disease in adults.
- It is not known if VUMERITY is safe and effective in children.

Do not take VUMERITY if you:

- have had an allergic reaction (such as welts, hives, swelling of the face, lips, mouth or tongue, or difficulty breathing) to diroximel fumarate, dimethyl fumarate, or any of the ingredients in VUMERITY. See “What are the ingredients in VUMERITY?” below for a complete list of ingredients.
- are taking dimethyl fumarate.

Before taking and while you take VUMERITY, tell your doctor about all of your medical conditions, including if you:

- have liver problems.
- have kidney problems.
- have or have had low white blood cell counts or an infection.
- are pregnant or plan to become pregnant. It is not known if VUMERITY will harm your unborn baby.
  - If you become pregnant while taking VUMERITY, talk to your healthcare provider about enrolling in the VUMERITY Pregnancy Registry. You can enroll in this registry by calling 1-833-569-2635 or visiting www.vumeritypregnancyregistry.com. The purpose of this registry is to monitor the health of you and your baby.
- are breastfeeding or plan to breastfeed. It is not known if VUMERITY passes into your breast milk. Talk to your healthcare provider about the best way to feed your baby while using VUMERITY.

Tell your doctor about all the medicines you take including prescription and over-the-counter medicines, vitamins, and herbal supplements.

How should I take VUMERITY?

- Take VUMERITY exactly as your doctor tells you to take it.
- The recommended starting dose on days 1 to 7 is one capsule by mouth 2 times a day. After 7 days, the recommended dose is 2 capsules by mouth 2 times a day.
- If taken with food, avoid taking VUMERITY with a high-fat, high-calorie meal or snack.
  - Your meal or snack should contain no more than 700 calories and no more than 30 g of fat.
- Swallow VUMERITY whole. Do not crush, chew, or sprinkle capsule contents on food.
- If you take too much VUMERITY, call your doctor or go to the nearest hospital emergency room right away.

What should I avoid while taking VUMERITY?

- Do not drink alcohol at the time you take a VUMERITY dose.

What are the possible side effects of VUMERITY?
VUMERITY may cause serious side effects including:

- allergic reaction (such as welts, hives, swelling of the face, lips, mouth or tongue, or difficulty breathing). Stop taking VUMERITY and get emergency medical help right away if you get any of these symptoms.
- PML (progressive multifocal leukoencephalopathy) a rare brain infection that usually leads to death or severe disability over a period of weeks or months. Tell your doctor right away if you get any of these symptoms of PML:

- weakness on one side of the body that gets worse
- vision problems
- confusion

- clumsiness in your arms or legs
- changes in thinking and memory
- personality changes

- herpes zoster infections (shingles), including central nervous system infections.
- other serious infections
- decreases in your white blood cell count. Your doctor should do a blood test to check your white blood cell count before you start treatment with VUMERITY and while you are on therapy. You should have blood tests after 6 months of treatment and every 6 to 12 months after that.
- liver problems. Your doctor should do blood tests to check your liver function before you start taking VUMERITY and during treatment if needed. Tell your doctor right away if you get any of these symptoms of a liver problem during treatment.
  - severe tiredness
  - loss of appetite
  - pain on the right side of your stomach
  - have dark or brown (tea color) urine
  - yellowing of your skin or the white part of your eyes
- serious gastrointestinal problems, including bleeding, ulcers, blockage, and tears (perforation) of the stomach or intestines. Tell your healthcare provider right away if you have any of these symptoms during treatment:
  - Stomach-area pain that does not go away
  - Bright red or black stools (that look like tar)
  - Severe vomiting
  - Severe diarrhea
  - Coughing up blood or blood clots
  - Vomiting blood or your vomit looks like "coffee grounds"

The most common side effects of VUMERITY include:

- flushing, redness, itching, or rash
- nausea, vomiting, diarrhea, stomach pain, or indigestion. These events can be serious in some patients (see "VUMERITY may cause serious side effects including," above).
- Flushing and stomach problems are the most common reactions, especially at the start of therapy, and may decrease over time. Taking VUMERITY with food (avoid high-fat, high-calorie meal or snack) may help reduce flushing. Call your doctor if you have any of these symptoms and they bother you or do not go away. Ask your doctor if taking aspirin before taking VUMERITY may reduce flushing.

These are not all the possible side effects of VUMERITY. Call your doctor for medical advice about side effects. You may report side effects to FDA at 1-800-FDA-1088.
For more information go to dailymed.nlm.nih.gov

How should I store VUMERITY?

- Store VUMERITY at room temperature between 68°F to 77°F (20°C to 25°C).
- Keep VUMERITY and all medicines out of the reach of children.

General Information about the safe and effective use of VUMERITY
Medicines are sometimes prescribed for purposes other than those listed in this Patient Information. Do not use VUMERITY for a condition for which it was not prescribed. Do not give VUMERITY to other people, even if they have the same symptoms that you have. It may harm them.
If you would like more information, talk to your doctor or pharmacist. You can ask your pharmacist or doctor for information about VUMERITY that is written for healthcare professionals.

What are the ingredients in VUMERITY?
Active ingredient: diroximel fumarate
Inactive ingredients: crospovidone, colloidal silicon dioxide, magnesium stearate (non-bovine), methacrylic acid and ethyl acrylate copolymer, microcrystalline cellulose, talc, and triethyl citrate. Capsule Shell: carrageenan, hypromellose, potassium chloride, and titanium dioxide. Capsule Shell Ink: iron oxide, potassium hydroxide, propylene glycol, and shellac.
Manufactured for: Biogen Inc., Cambridge, MA 02142, www.VUMERITY.com or call 1-800-456-2255

This Patient Information has been approved by the U.S. Food and Drug Administration.

Revised: 03/2024

PPI-54499-03

Principal Display Panel – 120 Capsule Carton Label

120
Capsules

RX Only

NDC 64406-020-03

VUMERITY™
(diroximel fumarate)
delayed-release capsules

231 mg

Swallow capsule whole.

Manufactured for:

Biogen Inc.
Cambridge, MA 02142

Product of the
United Kingdom.

Biogen®

Principal Display Panel – 120 Capsule Bottle Label

120
Capsules

RX Only

NDC 64406-020-03

VUMERITY™
(diroximel fumarate)
delayed-release capsules

231 mg

Swallow capsule whole.

Each capsule contains 231 mg
of diroximel fumarate.

Information and support:

1-800-456-2255

VUMERITY.com

Biogen®

120
Capsules